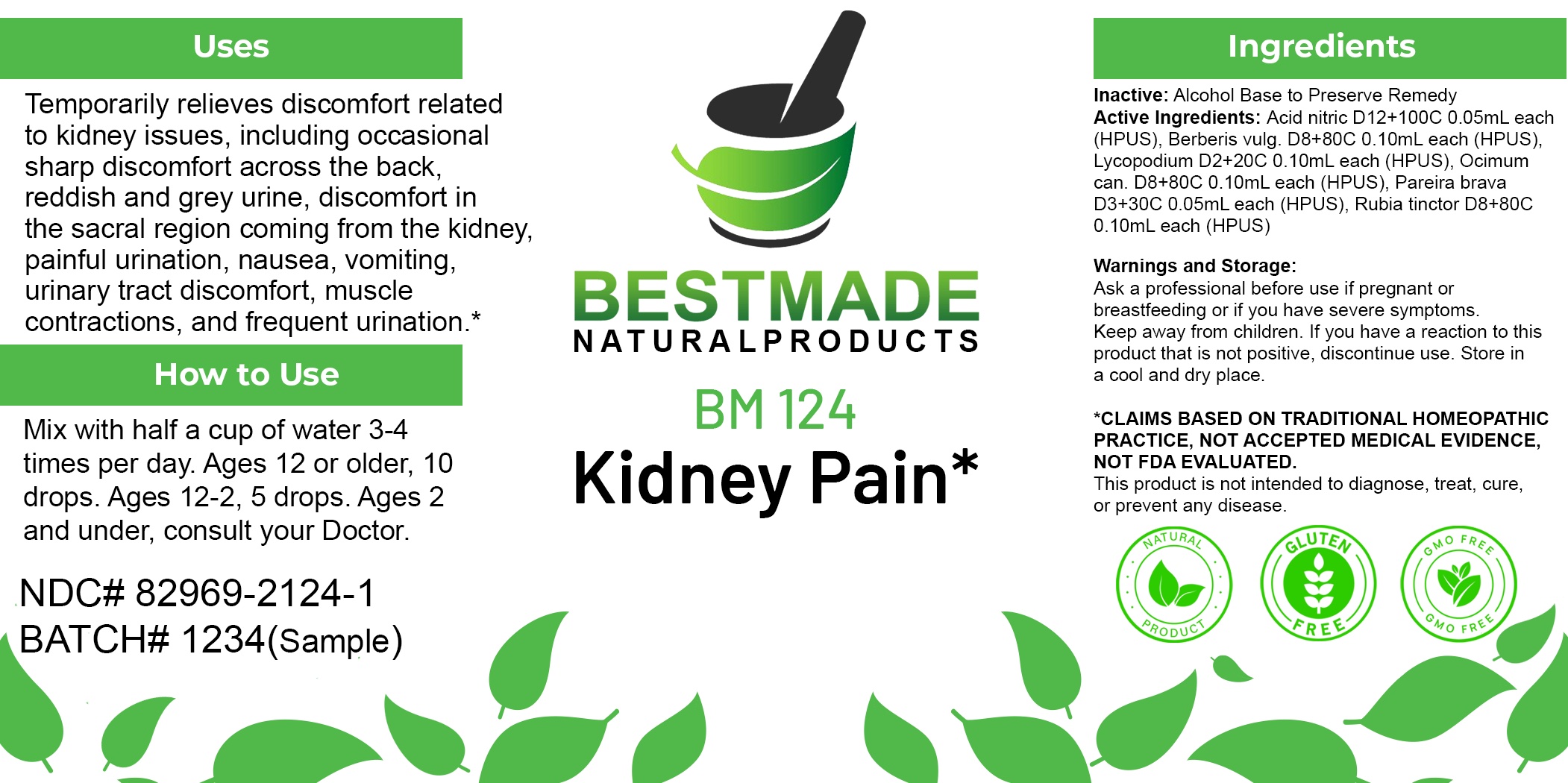 DRUG LABEL: Bestmade Natural Products BM124
NDC: 82969-2124 | Form: LIQUID
Manufacturer: Bestmade Natural Products
Category: homeopathic | Type: HUMAN OTC DRUG LABEL
Date: 20250210

ACTIVE INGREDIENTS: NITRIC ACID 30 [hp_C]/30 [hp_C]; BERBERIS VULGARIS ROOT BARK 30 [hp_C]/30 [hp_C]; OCIMUM AMERICANUM LEAF 30 [hp_C]/30 [hp_C]; LYCOPODIUM CLAVATUM SPORE 30 [hp_C]/30 [hp_C]; RUBIA TINCTORUM ROOT 30 [hp_C]/30 [hp_C]; CHONDRODENDRON TOMENTOSUM ROOT 30 [hp_C]/30 [hp_C]
INACTIVE INGREDIENTS: ALCOHOL 30 [hp_C]/30 [hp_C]

BM124

DOSAGE AND ADMINISTRATION

How to Use

Mix with half a cup of water 3-4 times per day. Ages 12 or older, 10 drops. Ages 12-2, 5 drops. Ages 2 and under, consult your Doctor.

Inactive:

Alcohol Base to Preserve Product

ACTIVE INGREDIENTS IN KIDNEY PAIN REMEDY

Acid nitric D12+100C 0.05mL each (HPUS), Berberis vulg. D8+80C 0.10mL each (HPUS), Lycopodium D2+20C 0.10mL each (HPUS), Ocimum can. D8+80C 0.10mL each (HPUS), Pareira brava D3+30C 0.05mL each (HPUS), Rubia tinctor D8+80C 0.10mL each (HPUS)

Uses
Temporarily relieves discomfort related to kidney issues, including occasional sharp discomfort across the back, reddish and grey urine, discomfort in the sacral region coming from the kidney, painful urination, nausea, vomiting, urinary tract discomfort, muscle contractions, and frequent urination.*

Uses
Temporarily relieves discomfort related to kidney issues, including occasional sharp discomfort across the back, reddish and grey urine, discomfort in the sacral region coming from the kidney, painful urination, nausea, vomiting, urinary tract discomfort, muscle contractions, and frequent urination.*

KEEP OUT OF REACH OF CHILDREN

Warnings and Storage:

Ask a professional before use if pregnant or breastfeeding or if you have severe symptoms.

Keep away from children. If you have a reaction to this product that is not positive, discontinue use. Store in a cool and dry place

*CLAIMS BASED ON TRADITIONAL HOMEOPATHIC PRACTICE, NOT ACCEPTED MEDICAL EVIDENCE NOT FDA EVALUATED.
This product is not intended to diagnose, treat, cure, or prevent any disease.

Warnings and Storage:

Ask a professional before use if pregnant or breastfeeding or if you have severe symptoms.

Keep away from children. If you have a reaction to this product that is not positive, discontinue use. Store in a cool and dry place

*CLAIMS BASED ON TRADITIONAL HOMEOPATHIC PRACTICE, NOT ACCEPTED MEDICAL EVIDENCE NOT FDA EVALUATED.
This product is not intended to diagnose, treat, cure, or prevent any disease.

Entire package label